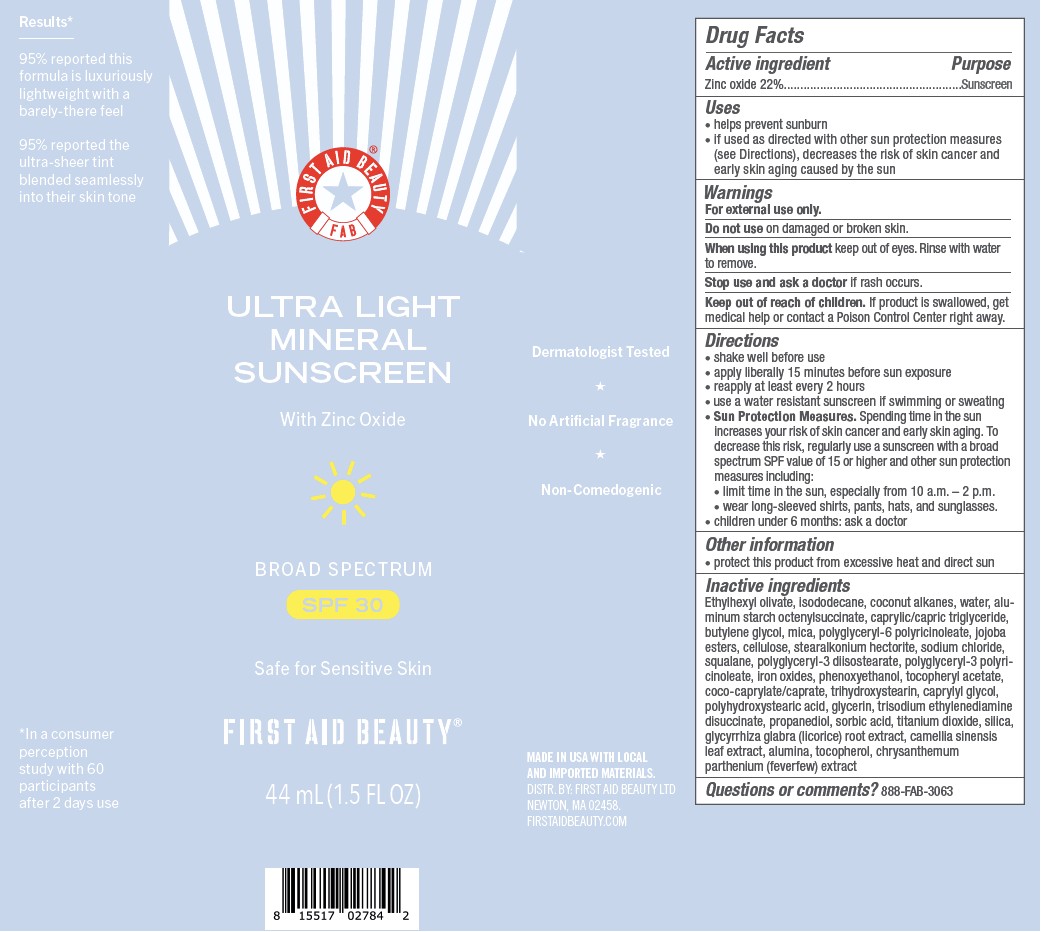 DRUG LABEL: First Aid Beauty FAB Ultra Light Mineral Sunscreen Broad Spectrum SPF 30
NDC: 84126-214 | Form: LIQUID
Manufacturer: The Procter & Gamble Manufacturing Company
Category: otc | Type: HUMAN OTC DRUG LABEL
Date: 20251209

ACTIVE INGREDIENTS: ZINC OXIDE 22 g/100 mL
INACTIVE INGREDIENTS: ETHYLHEXYL OLIVATE; FERROUS OXIDE; POWDERED CELLULOSE; TANACETUM PARTHENIUM WHOLE; POLYGLYCERYL-10 POLYRICINOLEATE; CAPRYLIC/CAPRIC TRIGLYCERIDE; WATER; GLYCERIN; CAMELLIA SINENSIS LEAF; GLYCYRRHIZA GLABRA (LICORICE) ROOT; PHENOXYETHANOL; POLYHYDROXYSTEARIC ACID (2300 MW); ALUMINA; MICA; COCO-CAPRYLATE/CAPRATE; COCONUT ALKANES; ISODODECANE; POLYGLYCERYL-3 DIISOSTEARATE; SILICA; TITANIUM DIOXIDE; TRIHYDROXYSTEARIN; CAPRYLYL GLYCOL; ALUMINUM STARCH OCTENYLSUCCINATE; BUTYLENE GLYCOL; SQUALANE; POLYGLYCERYL-6 POLYRICINOLEATE; STEARALKONIUM HECTORITE; PROPANEDIOL; TRISODIUM ETHYLENEDIAMINE DISUCCINATE; SODIUM CHLORIDE; SORBIC ACID; TOCOPHEROL; .ALPHA.-TOCOPHEROL ACETATE, DL-

First Aid Beauty FAB Ultra Light Mineral Sunscreen Broad Spectrum Sunscreen SPF 30

Drug Facts

ACTIVE INGREDIENT

Zinc oxide 22%

PURPOSE

Sunscreen

Uses

- helps prevent sunburn
- if used as directed with other sun protection measures (see Directions), decreases the risk of skin cancer and early skin aging caused by the sun

Warnings

For external use only

Do not use

- on damaged or broken skin

When using this product

- keep out of eyes. Rinse with water to remove.

Stop use and ask a doctor if

- rash occurs

Keep out of reach of children. If product is swallowed, get medical help or contact a Poison Control Center right away.

Directions

- shake well before use
- apply liberally 15 minutes before sun exposure
- reapply at least every 2 hours
- use water resistant sunscreen if swimming or sweating
- Sun Protection Measures. Spending time in the sun increases your risk of skin cancer and early skin aging. To decrease this risk, regularly use a sunscreen with a Broad Spectrum SPF value of 15 or higher and other sun protection measures including:
  - limit time in sun, especially from 10 a.m. - 2 p.m.
  - wear long-sleeved shirts, pants, hats, and sunglasses
- children under 6 months: ask a doctor

Other information

- protect this product from excessive heat and direct sun

Inactive ingredients

Ethylhexyl olivate, isododecane, coconut alkanes, water, aluminum starch octenylsuccinate, caprylic/capric triglyceride, butylene glycol, mica, polyglyceryl-6 polyricinoleate, jojoba esters, cellulose, stearalkonium hectorite, sodium chloride, squalane, polyglyceryl-3 diisostearate, polyglyceryl-3 polyricinoleate, iron oxides, phenoxyethanol, tocopheryl acetate, coco-caprylate/caprate, trihydroxystearin, caprylyl glycol, polyhydroxystearic acid, glycerin, trisodium ethylenediamine disuccinate, propanediol, sorbic acid, titanium dioxide, silica, glycyrrhiza glabra (licorice) root extract, camellia sinensis leaf extract, alumina, tocopherol, chrysanthemum parthenium (feverfew) extract

Questions?

888-FAB-3063

MADE IN USA.

FIRST AID BEAUTY ® LTD
NEWTON, MA 02458.

WWW.FIRSTAIDBEAUTY.COM

PACKAGE LABEL

FIRST AID BEAUTY ®

FAB

Ultra Light

Mineral

Sunsceren

with Zinc Oxide

Broad Spectrum SPF 30

1.5 FL OZ (44 mL)